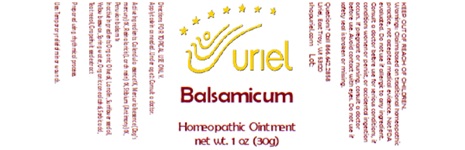 DRUG LABEL: Balsamicum
NDC: 48951-2159 | Form: OINTMENT
Manufacturer: Uriel Pharmacy, Inc
Category: homeopathic | Type: HUMAN OTC DRUG LABEL
Date: 20250110

ACTIVE INGREDIENTS: BALSAM PERU 1 [hp_X]/1 g; LARIX DECIDUA RESIN 1 [hp_X]/1 g; MERCURIALIS PERENNIS 1 [hp_X]/1 g; CALENDULA OFFICINALIS FLOWERING TOP 1 [hp_X]/1 g; ANTIMONY 1 [hp_X]/1 g
INACTIVE INGREDIENTS: SORBIC ACID; OLIVE OIL; SUNFLOWER OIL; WATER; LANOLIN; BEESWAX; ALCOHOL; TEA TREE OIL; CITRUS PARADISI SEED

Balsamicum

INDICATIONS AND USAGE

Directions: FOR TOPICAL USE ONLY.

DOSAGE AND ADMINISTRATION

Apply to skin as needed. Under age 2: Consult a doctor.

ACTIVE INGREDIENT

Active Ingredients: Calendula essence 1X, Mercurialis essence (Dog’s mercury) 1X, Resina laricis (Larch resin) 1X, Stibium (Antimony) 1X, Peruvian balsam 1x

INACTIVE INGREDIENT

Inactive Ingredients: Organic Olive oil, Lanolin, Sunflower seed oil, Yellow beeswax, Spring water, Organic cane alcohol, Sorbic acid, Tea tree oil, Grapefruit seed extract

Prepared using rhythmical processes.

PURPOSE

Uses: Temporary relief of minor wounds.

KEEP OUT OF REACH OF CHILDREN.

WARNINGS

Warnings: Claims based on traditional homeopathic practice, not accepted medical evidence. Not FDA evaluated. Do not use if allergic to any ingredient. Consult a doctor before use for serious conditions, if conditions worsen or persist, or accidental ingestion occurs. If pregnant or nursing, consult a doctor before use. Avoid contact with eyes. Do not use if safety seal is broken or missing.

Questions? Call 866.642.2858
Uriel, East Troy, WI 53120
shopuriel.com Lot: